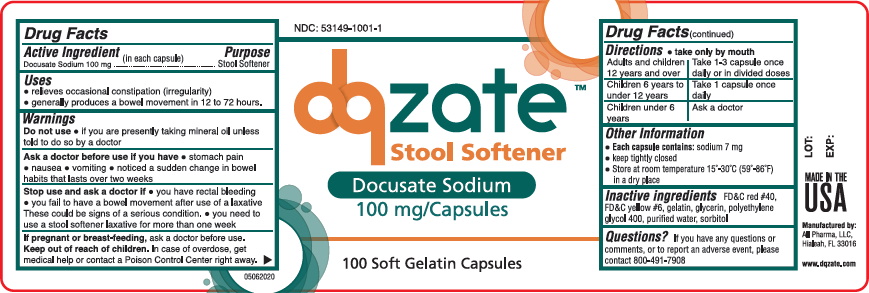 DRUG LABEL: DQZATE STOOL SOFTENER
NDC: 53149-1001 | Form: CAPSULE, GELATIN COATED
Manufacturer: All Pharma LLC
Category: otc | Type: HUMAN OTC DRUG LABEL
Date: 20201016

ACTIVE INGREDIENTS: DOCUSATE SODIUM 100 mg/1 1
INACTIVE INGREDIENTS: FD&C RED NO. 40; FD&C YELLOW NO. 6; GELATIN; GLYCERIN; POLYETHYLENE GLYCOL, UNSPECIFIED; WATER; SORBITOL

DQZATE Stool Softner

Warnings

Do Not use if you are presently taking mineral oils unless told to do so by a doctor.

Active ingredient (in each softgel)

Docusate Sodium 100 mg

Purpose

Stool softener laxative

Uses

relief of occasional constipation (irregularity)

generally produces bowel movement in 12 to 72 hours

If pregnant or breast-feeding

ask a doctor before use.

Keep out of reach of children.

In case of overdose, get medical help or contact a Poison Control Center right away.

Stop use and ask a doctor

If you have rectal bleeding

If you fail to have bowel movement after use of a laxative

If you need to use a stool softner laxative for more than a week

Directions

Adults and children 12 years and over:Take 1-3 Capsules once daily or in divided doses.

Children 6 years to under 12:Take one capsule once a day.

Children under 6 years: Ask your Doctor.

Other information

each softgel contains: sodium 7 mg

keep tightlyl closed

store at room temperature 15°-30°C (59°-86°F) in a dry place

Inactive ingredients

FD&C Red #40, FD&C Yellow #6, gelatin, glycerin, polyethylene glycol, sorbitol,purified water

DQZate

Label